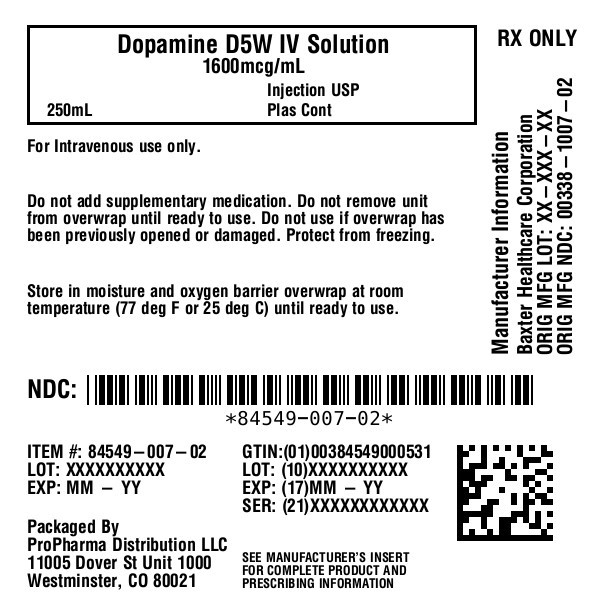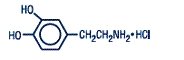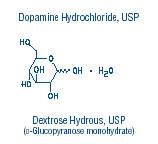 DRUG LABEL: Dopamine Hydrochloride and Dextrose
NDC: 84549-007 | Form: INJECTION, SOLUTION
Manufacturer: ProPharma Distribution
Category: prescription | Type: HUMAN PRESCRIPTION DRUG LABEL
Date: 20251218

ACTIVE INGREDIENTS: DOPAMINE HYDROCHLORIDE 160 mg/100 mL
INACTIVE INGREDIENTS: HYDROCHLORIC ACID; SODIUM BISULFITE 0.5 meq/100 mL; WATER; DEXTROSE MONOHYDRATE 5 g/100 mL

DOPamine Hydrochloride and 5% Dextrose Injection, USP
in Plastic Container
VIAFLEX Plus Container

DESCRIPTION

Dopamine Hydrochloride and 5% Dextrose Injection, USP is a sterile, nonpyrogenic solution of Dopamine Hydrochloride, USP and Dextrose, USP in Water for Injection. Structural formulas are shown below:

Dopamine Hydrochloride and 5% Dextrose Injection, USP is intended for intravenous use only. It contains no antimicrobial agents. The pH is adjusted with hydrochloric acid and is 3.5 (2.5 to 4.5). Approximately 5 mEq/L sodium bisulfite is added as a stabilizer. The solution provides a caloric content of 170 kcal/L. The solution is intended for single use only. When smaller doses are required, the unused portion should be discarded. Composition and osmolarity are given below:

800 mcg/mL Dopamine Hydrochloride and 5% Dextrose Injection, USPprovides 800 mcg/mL Dopamine Hydrochloride, USP and 50 g/L Dextrose Hydrous, USP with an osmolarity of 261 mOsmol/L (calc).

1600 mcg/mL Dopamine Hydrochloride and 5% Dextrose Injection, USPprovides 1600 mcg/mL Dopamine Hydrochloride, USP and 50 g/L Dextrose Hydrous, USP with an osmolarity of 269 mOsmol/L (calc).

3200 mcg/mL Dopamine Hydrochloride and 5% Dextrose Injection, USPprovides 3200 mcg/mL Dopamine Hydrochloride, USP and 50 g/L Dextrose Hydrous, USP with an osmolarity of 286 mOsmol/L (calc).

Dopamine administered intravenously is a myocardial inotropic agent which also may increase mesenteric and renal blood flow plus urinary output.

Dopamine hydrochloride is designated chemically as 3,4-dihydroxyphenethylamine hydrochloride, a white crystalline powder freely soluble in water. Dopamine (also referred to as 3-hydroxytyramine) is a naturally occurring biochemical catecholamine precursor of norepinephrine.

This VIAFLEX Plus plastic container is fabricated from a specially formulated polyvinyl chloride (PL 2207 Plastic). VIAFLEX containers, including VIAFLEX Plus containers, are made of flexible plastic and are for parenteral use. VIAFLEX Plus on the container indicates the presence of a drug additive in a drug vehicle. The amount of water that can permeate from inside the container into the overwrap is insufficient to affect the solution significantly. Solutions in contact with the plastic container can leach out certain of its chemical components in very small amounts within the expiration period, e.g., di-2-ethylhexyl phthalate (DEHP), up to 5 parts per million. However, the safety of the plastic has been confirmed in tests in animals according to USP biological tests for plastic containers as well as by tissue culture toxicity studies.

CLINICAL PHARMACOLOGY

Dopamine is a natural catecholamine formed by the decarboxylation of 3,4-dihydroxyphenylalanine (DOPA). It is a precursor to norepinephrine in noradrenergic nerves and is also a neurotransmitter in certain areas of the central nervous system, especially in the nigrostriatal tract, and in a few peripheral sympathetic nerves.

Dopamine produces positive chronotropic and inotropic effects on the myocardium, resulting in increased heart rate and cardiac contractility. This is accomplished directly by exerting an agonist action on beta-adrenoceptors and indirectly by causing release of norepinephrine from storage sites in sympathetic nerve endings.

Dopamine’s onset of action occurs within five minutes of intravenous administration, and with dopamine’s plasma half-life of about two minutes, the duration of action is less than ten minutes. If monoamine oxidase (MAO) inhibitors are present, however, the duration may increase to one hour. The drug is widely distributed in the body but does not cross the blood-brain barrier to a significant extent. Dopamine is metabolized in the liver, kidney, and plasma by MAO and catechol-O-methyltransferase to the inactive compounds homovanillic acid (HVA) and 3,4-dihydroxyphenylacetic acid. About 25% of the dose is taken up into specialized neurosecretory vesicles (the adrenergic nerve terminals), where it is hydroxylated to form norepinephrine. It has been reported that about 80% of the drug is excreted in the urine within 24 hours, primarily as HVA and its sulfate and glucuronide conjugates and as 3,4-dihydroxyphenylacetic acid. A very small portion is excreted unchanged.

The predominant effects of dopamine are dose-related, although actual response of an individual patient will largely depend on the clinical status of the patient at the time the drug is administered. At low rates of infusion (0.5-2 mcg/kg/min) dopamine causes vasodilation that is presumed to be due to a specific agonist action on dopamine receptors (distinct from alpha- and beta-adrenoceptors) in the renal, mesenteric, coronary, and intracerebral vascular beds. At these dopamine receptors, haloperidol is an antagonist. The vasodilation in these vascular beds is accompanied by increased glomerular filtration rate, renal blood flow, sodium excretion, and urine flow. Hypotension sometimes occurs. An increase in urinary output produced by dopamine is usually not associated with a decrease in osmolarity of the urine.

At intermediate rates of infusion (2-10 mcg/kg/min) dopamine acts to stimulate the beta1-adrenoceptors, resulting in improved myocardial contractility, increased SA rate and enhanced impulse conduction in the heart. There is little, if any, stimulation of the beta2-adrenoceptors (peripheral vasodilation). Dopamine causes less increase in myocardial oxygen consumption than isoproterenol, and its use is not usually associated with a tachyarrhythmia. Clinical studies indicate that it usually increases systolic and pulse pressure with either no effect or a slight increase in diastolic pressure. Blood flow to the peripheral vascular beds may decrease while mesenteric flow increased due to increased cardiac output. At low and intermediate doses, total peripheral resistance (which would be raised by alpha activity) is usually unchanged.

At higher rates of infusion (10-20 mcg/kg/min) there is some effect on alpha-adrenoceptors, with consequent vasoconstrictor effects and a rise in blood pressure. The vasoconstrictor effects are first seen in the skeletal muscle vascular beds, but with increasing doses they are also evident in the renal and mesenteric vessels. At very high rates of infusion (above 20 mcg/kg/min), stimulation of alpha-adrenoceptors predominates and vasoconstriction may compromise the circulation of the limbs and override the dopaminergic effects of dopamine, reversing renal dilation and natriuresis.

Dextrose provides a source of calories. Dextrose is readily metabolized, may decrease losses of body protein and nitrogen, promotes glycogen deposition and decreases or prevents ketosis if sufficient doses are provided.

INDICATIONS AND USAGE

Dopamine hydrochloride is indicated for the correction of hemodynamic imbalances present in the shock syndrome due to myocardial infarctions, trauma, endotoxic septicemia, open heart surgery, renal failure and chronic cardiac decompensation as in congestive failure.

Where appropriate, restoration of blood volume with a suitable plasma expander or whole blood should be instituted or completed prior to administration of dopamine hydrochloride.

Patients most likely to respond adequately to dopamine hydrochloride are those in whom physiological parameters, such as urine flow, myocardial function and blood pressure have not undergone profound deterioration. Reports indicate that the shorter the time interval between onset of signs and symptoms and initiation of therapy with volume correction and dopamine hydrochloride, the better the prognosis.

Poor Perfusion of Vital Organs

Urine flow appears to be one of the better diagnostic signs by which adequacy of vital organ perfusion can be monitored. Nevertheless, the physician should also observe the patient for signs of reversal of confusion or comatose condition. Loss of pallor, increase in toe temperature and/or adequacy of nail bed capillary filling may also be used as indices of adequate dosage. Reported studies indicate that when dopamine hydrochloride is administered before urine flow has diminished to levels of approximately 0.3 mL/minute, prognosis is more favorable. Nevertheless, in a number of oliguric or anuric patients, administration of dopamine hydrochloride has resulted in an increase in urine flow which in some cases reached normal levels. Dopamine hydrochloride may also increase urine flow in patients whose output is within normal limits and thus may be of value in reducing the degree of preexisting fluid accumulation. It should be noted that at doses above those optimal for the individual patient, urine flow may decrease, necessitating reduction of dosage. Concurrent administration of dopamine hydrochloride and diuretic agents may produce an additive or potentiating effect.

Low Cardiac Output

Increased cardiac output is related to dopamine hydrochloride’s direct inotropic effect on the myocardium. Increased cardiac output at low or moderate doses appears to be related to a favorable prognosis. Increase in cardiac output has been associated with either static or decreased systemic vascular resistance (SVR). Static or decreased SVR associated with low or moderate increments in cardiac output is believed to be a reflection of differential effects on specific vascular beds with increased resistance in peripheral beds (e.g., femoral) and concomitant decreases in mesenteric and renal vascular beds. Redistribution of blood flow parallels these changes so that an increase in cardiac output is accompanied by an increase in mesenteric and renal blood flow. In many instances the renal fraction of the total cardiac output has been found to increase. Increase in cardiac output produced by dopamine hydrochloride is not associated with substantial decreases in systemic vascular resistance as may occur with isoproterenol.

Hypotension

Hypotension due to inadequate cardiac output can be managed by administration of low to moderate doses of dopamine hydrochloride, which have little effect on SVR. At high therapeutic doses, dopamine hydrochloride’s alpha-adrenergic activity becomes more prominent and thus may correct hypotension due to diminished SVR. As in the case of other circulatory decompensation states, prognosis is better in patients whose blood pressure and urine flow have not undergone profound deterioration. Therefore, it is suggested that the physician administer dopamine hydrochloride as soon as a definite trend toward decreased systolic and diastolic pressure becomes evident.

CONTRAINDICATIONS

Dopamine hydrochloride should not be used in patients with pheochromocytoma.

Dopamine hydrochloride should not be administered in the presence of uncorrected tachyarrhythmias or ventricular fibrillation.

Solutions containing dextrose may be contraindicated in patients with known allergy to corn or corn products.

WARNINGS

Patients who have been treated with monoamine oxidase (MAO) inhibitors prior to the administration of dopamine hydrochloride will require substantially reduced dosage. See Drug Interactions, below.

Evidence is inadequate for fully defining proper dosage and limitations for use in children.

Contains sodium bisulfite, a sulfite that may cause allergic-type reactions including anaphylactic symptoms and life-threatening or less severe asthmatic episodes in certain susceptible people. The overall prevalence of sulfite sensitivity in the general population is unknown and probably low. Sulfite sensitivity is seen more frequently in asthmatic than in nonasthmatic people.

Do notadd Dopamine Hydrochloride and 5% Dextrose Injection, USP to any alkaline diluent solution since dopamine hydrochloride is inactivated in alkaline solution.

Solutions containing dextrose should not be administered through the same administration set as blood, as this may result in pseudoagglutination or hemolysis.

The intravenous administration of solutions may cause fluid overloading resulting in dilution of serum electrolyte concentrations, overhydration, congested states or pulmonary edema.

Excess administration of potassium-free solutions may result in significant hypokalemia.

PRECAUTIONS

General

Avoid bolus administration of dopamine hydrochloride. See DOSAGE AND ADMINISTRATION.

Avoid Hypovolemia

Prior to treatment with dopamine hydrochloride, hypovolemia should be fully corrected, if possible, with either whole blood, plasma, or plasma expanders as indicated. Monitoring of central venous pressure or left ventricular filling pressure may be helpful in detecting and treating hypovolemia.

Hypoxia, Hypercapnia, Acidosis

These conditions, which may also reduce the effectiveness and/or increase the incidence of adverse effects of dopamine, must be identified and corrected prior to, and concurrently with, administration of dopamine HCl.

Ventricular Arrhythmias

If an increased number of ectopic beats is observed, the dose should be reduced if possible.

Decreased Pulse Pressure

If a disproportionate rise in the diastolic pressure (i.e., marked decrease in the pulse pressure) is observed in patients receiving dopamine hydrochloride, the infusion rate should be decreased and the patient observed carefully for further evidence of predominant vasoconstrictor activity, unless such an effect is desired.

Hypotension

At lower infusion rates, if hypotension occurs, the infusion rate should be rapidly increased until adequate blood pressure is obtained. If hypotension persists, dopamine HCl should be discontinued and a more potent vasoconstrictor agent such as norepinephrine should be administered.

Occlusive Vascular Disease

Patients with a history of occlusive vascular disease (for example, atherosclerosis, arterial embolism, Raynaud’s disease, cold injury, diabetic endarteritis and Buerger’s disease) should be closely monitored for any changes in color or temperature of the skin in the extremities. If a change in skin color or temperature occurs and is thought to be the result of compromised circulation to the extremities, the benefits of continued dopamine hydrochloride infusion should be weighed against the risk of possible necrosis. This condition may be reversed by either decreasing the rate or discontinuing the infusion.

Extravasation

Dopamine Hydrochloride and 5% Dextrose Injection, USP should be infused into a large vein whenever possible to prevent the possibility of extravasation into tissue adjacent to the infusion site. Extravasation may cause necrosis and sloughing of surrounding tissue. Large veins of the antecubital fossa are preferred to veins in the dorsum of the hand or ankle. Less suitable infusion sites should be used only if the patient’s condition requires immediate attention. The physician should switch to more suitable sites as rapidly as possible. The infusion site should be continuously monitored for free flow.

IMPORTANT - Antidote for Peripheral Ischemia
To prevent sloughing and necrosis in ischemic areas, the area should be infiltrated as soon as possible with 10 to 15 mL of 0.9% Sodium Chloride Injection, USP containing from 5 to 10 mg phentolamine, an adrenergic blocking agent. A syringe with a fine hypodermic needle should be used and the solution liberally infiltrated throughout the ischemic area. Sympathetic blockage with phentolamine causes immediate and conspicuous local hyperemic changes if the area is infiltrated within 12 hours. Therefore, phentolamine should be given as soon as possible after the extravasation is noted.

Weaning

When discontinuing the infusion, it may be necessary to gradually decrease the dose of dopamine HCl while expanding blood volume with IV fluids, since sudden cessation may result in marked hypotension.

Careful Monitoring Required

Close monitoring of the following indices - urine flow, cardiac output and blood pressure - during dopamine hydrochloride infusion is necessary as in the case of any adrenergic agent.

Solutions containing dextrose should be used with caution in patients with known subclinical or overt diabetes mellitus.

Do not administer unless solution is clear and seal is intact.

If administration is controlled by a pumping device, care must be taken to discontinue pumping action before the container runs dry or air embolism may result.

Laboratory Tests

Clinical evaluation and periodic laboratory determinations are necessary to monitor changes in fluid balance, electrolyte concentrations and acid base balance during prolonged parenteral therapy or whenever the condition of the patient warrants such evaluation.

Drug Interactions

Cyclopropane or halogenated hydrocarbon anesthetics increase cardiac autonomic irritability and may sensitize the myocardium to the action of certain intravenously administered catecholamines, such as dopamine. This interaction appears to be related both to pressor activity and to the beta-adrenergic stimulating properties of these catecholamines, and may produce ventricular arrhythmias. Therefore, EXTREME CAUTION should be exercised when administering dopamine HCl to patients receiving cyclopropane or halogenated hydrocarbon anesthetics. Results of studies in animals indicate that dopamine-induced ventricular arrhythmias during anesthesia can be reversed by propranolol.

Because dopamine is metabolized by monoamine oxidase (MAO), inhibition of this enzyme prolongs and potentiates the effect of dopamine. Patients who have been treated with MAO inhibitors within two to three weeks prior to the administration of dopamine should receive initial doses of dopamine hydrochloride no greater than one-tenth (1/10) of the usual dose.

Concurrent administration of low-dose dopamine HCl and diuretic agents may produce an additive or potentiating effect on urine flow.

Tricyclic antidepressants may potentiate the cardiovascular effects of adrenergic agents.

Cardiac effects of dopamine are antagonized by beta-adrenergic blocking agents, such as propranolol and metoprolol. The peripheral vasoconstriction caused by high doses of dopamine HCl is antagonized by alpha-adrenergic blocking agents. Dopamine-induced renal and mesenteric vasodilation is not antagonized by either alpha- or beta-adrenergic blocking agents.

Butyrophenones (such as haloperidol) and phenothiazines can suppress the dopaminergic renal and mesenteric vasodilation induced with low-dose dopamine infusion.

The concomitant use of vasopressors, vasoconstrictor agents (such as ergonovine) and some oxytocic drugs may result in severe hypertension.

Administration of phenytoin to patients receiving dopamine HCl has been reported to lead to hypotension and bradycardia. It is suggested that in patients receiving dopamine HCl, alternatives to phenytoin should be considered if anticonvulsant therapy is needed.

Carcinogenesis, Mutagenesis, Impairment of Fertility

Long term animal studies have not been performed to evaluate the carcinogenic potential of dopamine HCl.

Dopamine HCl at doses approaching maximal solubility showed no clear genotoxic potential in the Ames test. Although there was a reproducible dose-dependent increase in the number of revertant colonies with strains TA100 and TA98, both with and without metabolic activation, the small increase was considered inconclusive evidence of mutagenicity. In the L5178Y TK ± mouse lymphoma assay, dopamine HCl at the highest concentrations used of 750 μg/ml without metabolic activation, and 3000 μg/ml with activation, was toxic and associated with increases in mutant frequencies when compared to untreated and solvent controls; at the lower concentrations no increases over controls were noted.

No clear evidence of clastogenic potential was reported in the in vivo mouse or male rat bone marrow micronucleus test when the animals were treated intravenously with up to 224 mg/kg and 30 mg/kg of dopamine HCl, respectively.

Pregnancy

Teratogenic Effects

Teratogenicity studies in rats and rabbits at dopamine HCl dosages up to 6 mg/kg/day intravenously during organogenesis produced no detectable teratogenic or embryotoxic effects, although maternal toxicity consisting of mortalities, decreased body weight gain, and pharmacotoxic signs were observed in rats. In a published study, dopamine HCl administered at 10 mg/kg subcutaneously for 30 days, markedly prolonged metestrus and increased mean pituitary and ovary weights in female rats. Similar administration to pregnant rats throughout gestation or for 5 days starting on gestation day 10 or 15 resulted in decreased body weight gains, increased mortalities and slight increases in cataract formation among the offspring. There are no adequate and well-controlled studies in pregnant women, and it is not known if dopamine HCl crosses the placental barrier. Dopamine HCl should be used during pregnancy only if the potential benefit justifies the potential risk to the fetus.

Labor and Delivery

In obstetrics, if vasopressor drugs are used to correct hypotension or are added to a local anesthetic solution the interaction with some oxytocic drugs may cause severe hypertension.

Nursing Mothers

It is not known whether dopamine hydrochloride is excreted in human milk. Because many drugs are excreted in human milk, caution should be exercised when dopamine hydrochloride is administered to a nursing woman.

Pediatric Use

Safety and effectiveness in children have not been established. The clearance of dopamine is affected by age (as much as 2 fold greater in children under 2 years of age), renal and hepatic function (decreasing by 2 fold in the presence of either). In younger children, particularly neonates, clearance is highly variable. Newborn infants may be more sensitive to the vasoconstrictive effects of dopamine.

The most consistent effects of dopamine in 57 publications (between the years 1966 through 1997) were increases in systolic and mean arterial pressure. Renal function was variably affected, except that in a single publication renal function was preserved in the face of treatment with indomethacin. No consistent effect on heart rate was described. Because of the variability of clearance, especially in the neonate and newborn, low doses of dopamine and slow deliberate titration should be employed (see DOSAGE and ADMINISTRATION).

Geriatric Use

Clinical studies of dopamine injection did not include sufficient numbers of subjects aged 65 and over to determine whether they respond differently from younger subjects. Other reported clinical experience has not identified differences in responses between the elderly and younger patients. In general, dose selection for an elderly patient should be cautious, usually starting at the low end of the dosing range, reflecting the greater frequency of decreased hepatic, renal, or cardiac function, and of concomitant disease or other drug therapy.

ADVERSE REACTIONS

The following adverse reactions have been observed, but there are not enough data to support an estimate of their frequency.

Cardiovascular System

ventricular arrhythmia

atrial fibrillation

ectopic beats

tachycardia

anginal pain

palpitation

cardiac conduction abnormalities

widened QRS complex

bradycardia

hypotension

hypertension

vasoconstriction

Respiratory System

dyspnea

Gastrointestinal System

nausea

vomiting

Metabolic/Nutritional System

azotemia

Central Nervous System

headache

anxiety

Dermatological System

piloerection

Other

Gangrene of the extremities has occurred when high doses were administered for prolonged periods or in patients with occlusive vascular disease receiving low doses of dopamine HCl.

OVERDOSAGE

In case of accidental overdosage, as evidenced by excessive blood pressure elevation, reduce rate of administration or temporarily discontinue dopamine hydrochloride until patient’s condition stabilizes. Since dopamine hydrochloride’s duration of action is quite short, no additional remedial measures are usually necessary. If these measures fail to stabilize the patient’s condition, use of the short-acting alpha-adrenergic blocking agent, phentolamine, should be considered.

DOSAGE AND ADMINISTRATION

Rate of Administration

Dopamine Hydrochloride and 5% Dextrose Injection, USP is administered intravenously through a suitable intravenous catheter or needle. An IV drip chamber or other suitable metering device is essential for controlling the rate of flow in drops/minute. Each patient must be individually titrated to the desired hemodynamic and/or renal response with dopamine hydrochloride. In titrating to the desired increase in systolic blood pressure, the optimum dosage rate for renal response may be exceeded, thus necessitating a reduction in rate after the hemodynamic condition is stabilized.

Administration of dopamine hydrochloride at rates greater than 50 mcg/kg/min has safely been used in advanced circulatory decompensation states. If unnecessary fluid expansion is of concern, use of a more concentrated solution may be preferred over increasing the flow rate of a less concentrated solution.

Suggested Regimen

1. When appropriate, increase blood volume with whole blood, plasma, or plasma expanders until central venous pressure is 10 to 15 cm H2O or pulmonary wedge pressure is 14 to 18 mm Hg.
2. Begin infusion of Dopamine Hydrochloride and 5% Dextrose Injection, USP at doses of 2 to 5 mcg/kg/min in patients who are likely to respond to modest increments of heart force and renal perfusion.
  In more seriously ill patients, begin administration of Dopamine Hydrochloride and 5% Dextrose Injection, USP at rates of 5 mcg/kg/min and increase gradually using 5 to 10 mcg/kg/min increments up to a rate of 20 to 50 mcg/kg/min as needed. If rates in excess of 50 mcg/kg/min are required, it is suggested that urine output be checked frequently. Should urine flow begin to decrease in the absence of hypotension, reduction of dopamine hydrochloride dosage should be considered. Reports have shown that more than 50% of the patients were satisfactorily maintained on doses of dopamine hydrochloride administered at rates of less than 20 mcg/kg/min. In patients who do not respond to these doses with adequate arterial pressures or urine flow, additional increments of dopamine hydrochloride may be given in an effort to produce an appropriate arterial pressure and central perfusion.
3. Treatment of all patients requires constant evaluation of therapy in terms of blood volume, augmentation of myocardial contractility and distribution of peripheral perfusion. Dosage of dopamine hydrochloride should be adjusted according to the patient’s response, with particular attention to diminution of established urine flow rate, increasing tachycardia or development of new dysrhythmias as indices for decreasing or temporarily suspending the dosage.
4. As with all potent intravenously administered drugs, care should be taken to control the rate of administration so as to avoid inadvertent administration of a bolus of drug.

Parenteral drug products should be inspected visually for particulate matter and discoloration prior to administration, whenever solution and container permit.

Do not use Dopamine Hydrochloride and 5% Dextrose Injection, USP if darker than slightly yellow or discolored in any other way.

All injections in VIAFLEX Plus plastic containers are intended for intravenous administration using sterile equipment.

Drug additives should not be made to Dopamine Hydrochloride and 5% Dextrose Injection, USP.

Pediatric Dosing and Administration

In publications, the most common starting doses were 1-5 micrograms/kilograms/minute. Particularly in neonates, such low doses require considerable dilution of this product; careful consideration should be given to the use of this product in such circumstances.Dosing increments that were reported ranged from 2.5 to 5.0 micrograms/kilogram/minute. Usual maximum doses were 15-20 micrograms/kilogram/minute, with occasional use as great as 50 micrograms/kilogram/minute. The time course of dopamine kinetics is poorly defined. Increasing infusion rates (or dose) should be approached cautiously and only after it is apparent that hemodynamics (mainly systolic blood pressure) have stabilized with respect to the current dose and/or rate of infusion.

There have been occasional reports of vasospastic events when dopamine was infused through umbilical vessels. Due caution should be exercised if infusion of dopamine through umbilical vessels becomes necessary.

HOW SUPPLIED

 | Size (mL) | mcg/mL | NDC
 | 250 | 1600 | 84549-007-02

Exposure of pharmaceutical products to heat should be minimized. Avoid excessive heat. Protect from freezing. It is recommended the product be stored at room temperature (25°C); brief exposure up to 40°C does not adversely affect the product.

Avoid contact with alkalies (including sodium bicarbonate), oxidizing agents or iron salts.

NOTE - Do not use the injection if it is darker than slightly yellow or discolored in any other way.

DIRECTIONS FOR USE OF VIAFLEX PLUS PLASTIC CONTAINER

The overwrap is a moisture and oxygen barrier. Do not remove unit from overwrap until ready for use. A sulfur dioxide odor may occur upon removal of the product from the overwrap container. The sulfur dioxide odor from Dopamine Injection does not pose risk to the clinician or patient using the product.

To open

Tear overwrap down side at notch and remove solution container. Some opacity of the plastic due to moisture absorption during the sterilization process may be observed. This is normal and does not affect the solution quality or safety. The opacity will diminish gradually. Check for minute leaks by squeezing inner bag firmly. If leaks are found, discard solution as sterility may be impaired.

PREPARATION FOR ADMINISTRATION

Visually inspect the container. If the administration port protector is damaged, detached, or not present, discard container as solution path sterility may be impaired.

Caution: Do not use plastic containers in series connections. Such use could result in air embolism due to residual air being drawn from the primary container before administration of the fluid from the secondary container is completed.

1. Suspend container from eyelet support.
2. Remove plastic protector from administration port at bottom of container.
3. Attach administration set. Refer to complete directions accompanying set.

Printed in USA

Baxter and Viaflex are trademarks of Baxter International Inc.